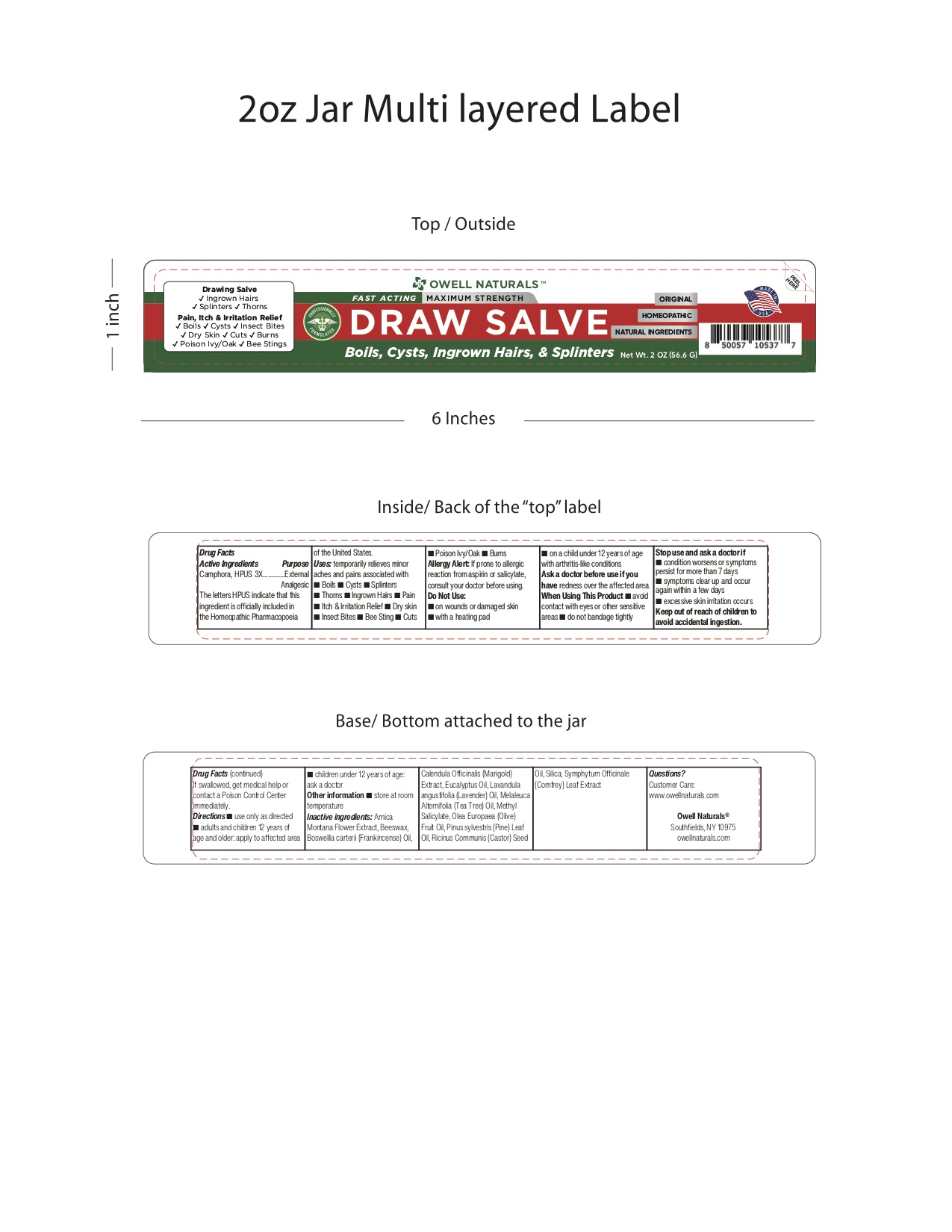 DRUG LABEL: Owell Naturals Draw Salve with Camphor 2.0 oz.
NDC: 83570-540 | Form: SALVE
Manufacturer: Owell Naturals Brand LLC
Category: homeopathic | Type: HUMAN OTC DRUG LABEL
Date: 20250912

ACTIVE INGREDIENTS: CAMPHOR (NATURAL) 1.132 g/56.6 g
INACTIVE INGREDIENTS: FRANKINCENSE OIL; METHYL SALICYLATE; COMFREY LEAF; SILICON DIOXIDE; ARNICA MONTANA FLOWER; WHITE WAX; CALENDULA OFFICINALIS FLOWER; LAVENDER OIL; TEA TREE OIL; WHITE PINE OIL; EUCALYPTUS OIL; OLIVE OIL; CASTOR OIL

Owell Naturals Draw Salve with Camphor 2.0 oz.

ACTIVE INGREDIENT

CAMPHORA [HPUS]

Uses

temporarily relieves minor aches and pains associated with

Boils

Cysts

Splinters

Thorns

Ingrown Hairs

Pain

Itch & Irritation Relief

Dry Skin

Insect Bites

Bee Sting

Cuts

Poison Ivy/Oak

Burns

Do not Use

on wounds or damaged skin

with a heating pad

on a child under 12 years of age with arthritis-like conditions

Ask a doctor before use if you have

redness over the affected area

When using this product

avoid contact with eyes or other sensitive areas

do not bandage tightly

Stop use and ask a doctor if

condition worsens or symptoms persist for more than 7 days

symptoms clear up and occur again within a few days

excessive skin irritation occurs

Keep out of reach of children to avoid accidental ingestion.

If swallowed, get medical help or contact a Poison Control Center immediately.

Directions

Use only as directed

adults and children 12 years of age and older, apply to affected area

children under 12 years of age, ask a doctor

OTHER SAFETY INFORMATION

store at room temperature

Questions?

Customer Care: www.owellnaturals.com

Inactive Ingredients

Arnica Montana Flower Extract, Beeswax, Boswellia carterii (Frankincense) Oil, Calendula Officinalis (Marigold) Extract, Eucalyptus Oil,

Lavandula angustifolia (Lavender) Oil, Melaleuca alternifolia (Tea Tree) Oil, Methyl Salicylate, Olea Europaea (Olive) Fruit Oil,

Pinus sylvestris (Pine) Leaf Oil, Ricinus communis (Castor) Seed Oil, Silica, Symphytum Officinale (Comfrey) Leaf Extract

PURPOSE

External Analgesic

Allergy Alert: If prone to allergic reaction from aspirin or salicylate, consult your doctor before using.

Do Not Use:

- on wounds or damaged skin
- with a heating pad
- on a child under 12 years of age with arthritis-like conditions

Stop use and ask a doctor if

- condition worsens or symptoms persist for more than 7 days
- symptoms clear up and occur again within a few days

RECENT MAJOR CHANGES

Uses No Major Changes. This is a Second product for this client.
Doses and Administration. No major changes

PACKAGE LABEL

Original 2 Oz RED GREEN CAMPHORA.jpg